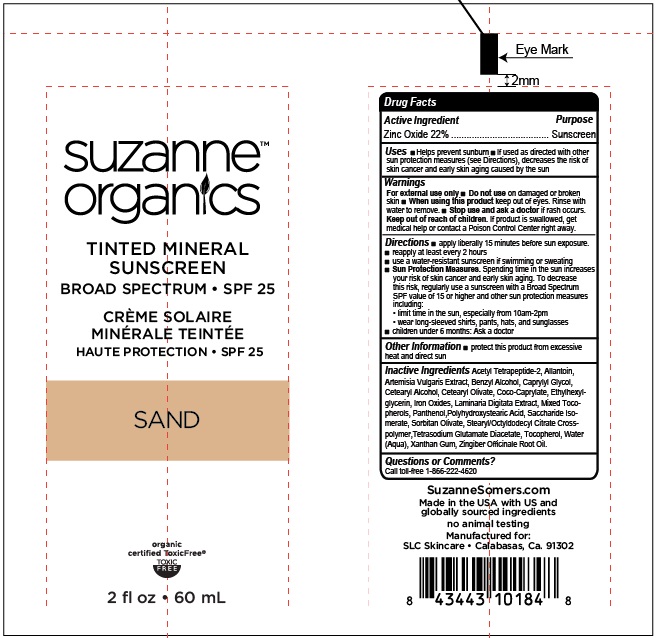 DRUG LABEL: Suzanne Organics Tinted Mineral Sunscreen Broad Spectrum SPF 25 - Sand
NDC: 15435-300 | Form: CREAM
Manufacturer: SLC Skincare
Category: otc | Type: HUMAN OTC DRUG LABEL
Date: 20231114

ACTIVE INGREDIENTS: ZINC OXIDE 220 mg/1 mL
INACTIVE INGREDIENTS: POLYHYDROXYSTEARIC ACID (2300 MW); GINGER OIL; ACETYL TETRAPEPTIDE-2; ALLANTOIN; BENZYL ALCOHOL; CAPRYLYL GLYCOL; CETOSTEARYL ALCOHOL; CETEARYL OLIVATE; COCO-CAPRYLATE; ETHYLHEXYLGLYCERIN; FERRIC OXIDE RED; LAMINARIA DIGITATA; PANTHENOL; SACCHARIDE ISOMERATE; SORBITAN OLIVATE; STEARYL/OCTYLDODECYL CITRATE CROSSPOLYMER; TETRASODIUM GLUTAMATE DIACETATE; TOCOPHEROL; WATER; XANTHAN GUM; ARTEMISIA VULGARIS ROOT

Suzanne Organics Tinted Mineral Sunscreen Broad Spectrum SPF 25 - Sand

Active Ingredient

Zinc Oxide 22%

Purpose

Sunscreen

Uses

- Helps prevent sunburn
- If used as directed with other sun protection measures (see Directions), decreases the risk of skin cancer and early skin aging caused by the sun

Warnings

- For external use only

Do not use

- on damaged or broken skin

When using this product

- keep out of eyes. Rinse with water to remove.

Stop use and ask a doctor

- if rash occurs.

Keep out of reach of children.

If product is swallowed, get medical help or contact a Poison Control Center right away.

Directions

- apply liberally 15 minutes before sun exposure.
- reapply at least every 2 hours
- use a water-resistant sunscreen if swimming or sweating
- Spending time in the sun increases your risk of skin cancer and early skin aging. To decrease this risk, regularly use a sunscreen with a Broad Spectrum SPF value of 15 or higher and other sun protection measures including: Sun Protection Measures.
- limit time in the sun, especially from 10am-2pm
- wear long-sleeved shirts, pants, hats, and sunglasses
- children under 6 months: Ask a doctor

Other Information

- protect this product from excessive heat and direct sun

Inactive Ingredients

Acetyl Tetrapeptide-2, Allantoin, Artemisia Vulgaris Extract, Benzyl Alcohol, Caprylyl Glycol, Cetearyl Alcohol, Cetearyl Olivate, Coco-Caprylate, Ethylhexylglycerin, Iron Oxides, Laminaria Digitata Extract, Mixed Tocopherols, Panthenol, Polyhydroxystearic Acid, Saccharide Isomerate, Sorbitan Olivate, Stearyl Octyldodecyl Citrate Crosspolymer, Tetrasodium Glutamate Diacetate, Tocopherol, Water (Aqua), Xanthan Gum, Zingiber Officinale Root Oil.

Questions or Comments?

Call toll free 1-866-222-4620